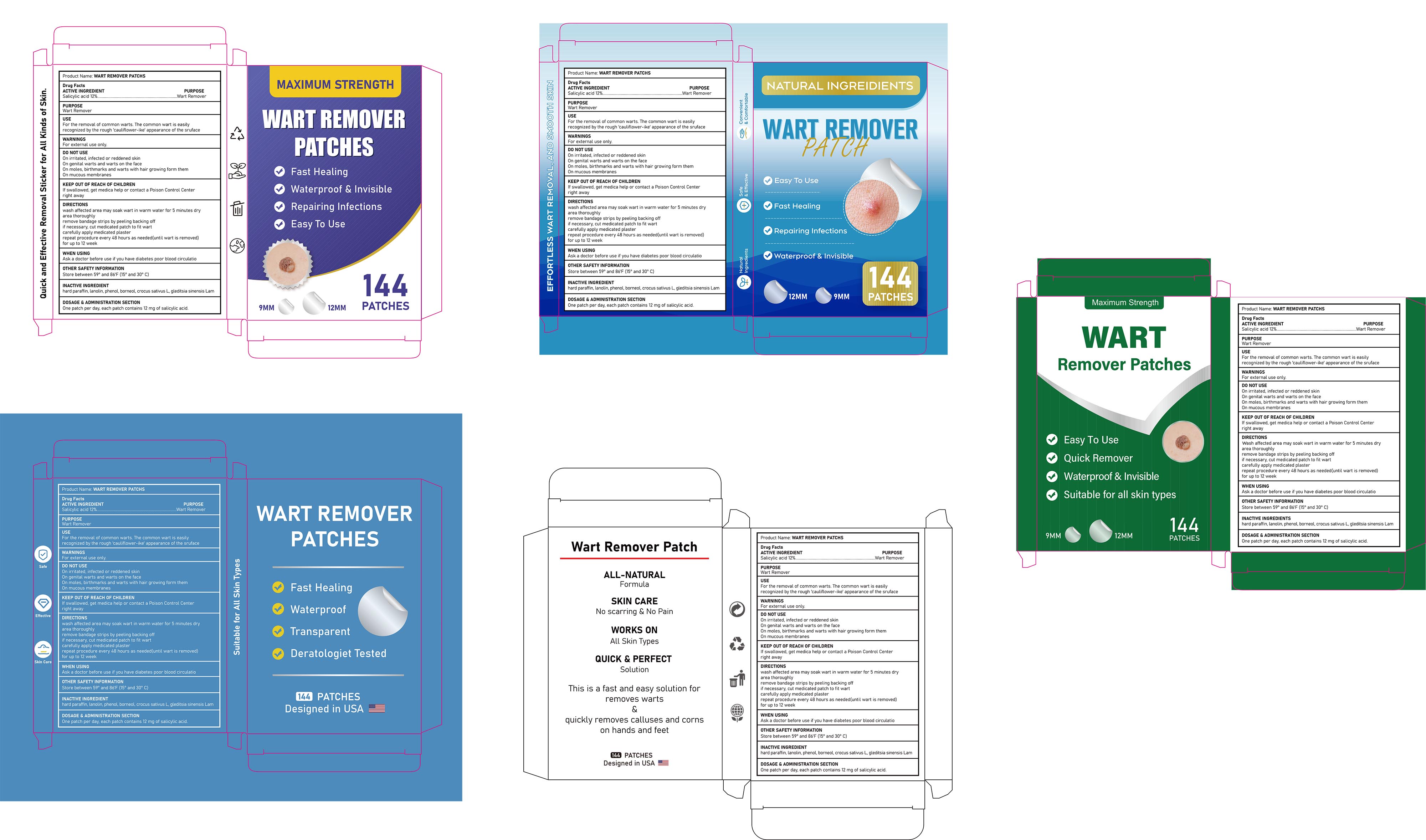 DRUG LABEL: Knee Pain Relief Patch
NDC: 85839-006 | Form: PATCH
Manufacturer: Shenzhen Finona Information Technology Co., Ltd
Category: otc | Type: HUMAN OTC DRUG LABEL
Date: 20251112

ACTIVE INGREDIENTS: METHYL SALICYLATE 0.063 g/1 1; LEVOMENTHOL 0.057 g/1 1; CAMPHOR (SYNTHETIC) 0.012 g/1 1
INACTIVE INGREDIENTS: CINNAMON; ORANGE PEEL; GLYCERIN; GINGER

85839-006 Knee Pain Relief Patch

ACTIVE INGREDIENT

DL-Camphor 1.2%
L-Menthol 5.7%
Methyl Salicylate 6.3%

PURPOSE

Topical Analgesic

INDICATIONS AND USAGE

For temporary relief of minor aches and pains of muscles and joints associated with:
Arthritis Strainsm Bruisesm Sprains

WARNINGS

For external use only.

DO NOT USE

If you are allergic to aspirin or salicylates.
With a heating pad.
With, or at the same time as, other external analgesic products

WHEN USING

Use only as directed

Avoid contact with the eyes, mucous membranes, or rashes

KEEP OUT OF REACH OF CHILDREN

If swallowed, get medical help or contact a Poison Control Center right away.

DOSAGE AND ADMINISTRATION

Clean and dry the affected area.
Remove a patch from the film.
Apply the patch to the affected area for not more than 3 to 4 times a day for 7 days.
You can wear the patch for up to 8 hours per application.
Adults and children 12 years of age and over: Consult a doctor

INACTIVE INGREDIENT

Dried Ginger
Cinnamon
Orange Peel
Glycerol